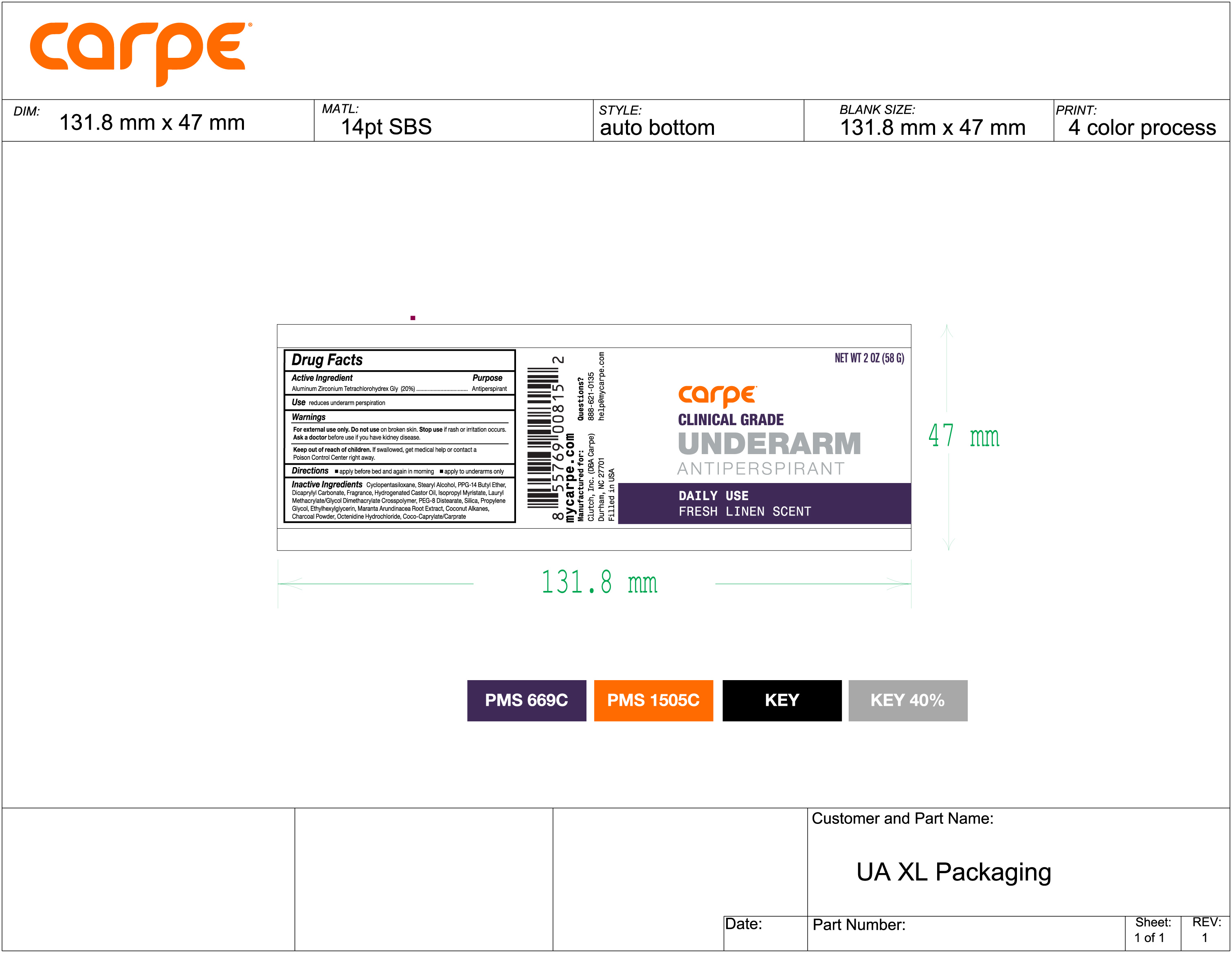 DRUG LABEL: Underarm Antiperspirant Daily Use Fresh Linen Scent
NDC: 74307-009 | Form: STICK
Manufacturer: Clutch Inc
Category: otc | Type: HUMAN OTC DRUG LABEL
Date: 20251211

ACTIVE INGREDIENTS: ALUMINUM ZIRCONIUM TETRACHLOROHYDREX GLY 20 g/100 g
INACTIVE INGREDIENTS: SILICON DIOXIDE; LAURYL METHACRYLATE/GLYCOL DIMETHACRYLATE CROSSPOLYMER; MARANTA ARUNDINACEA ROOT; DICAPRYLYL CARBONATE; PEG-8 DISTEARATE; PROPYLENE GLYCOL; ISOPROPYL MYRISTATE; HYDROGENATED CASTOR OIL; ISOPROPYL ALCOHOL; COCONUT ALKANES; CYCLOMETHICONE 5; OCTENIDINE HYDROCHLORIDE; PPG-14 BUTYL ETHER; COCO-CAPRYLATE/CAPRATE; ETHYLHEXYLGLYCERIN; ACTIVATED CHARCOAL; STEARYL ALCOHOL

Underarm Antiperspirant Daily Use
Fresh Linen Scent

Active Ingredient Purpose

Aluminum Zirconium Tetrachlorohydrex Gly (20%) Antiperspirant

Use

reduces underarm perspiration

KEEP OUT OF REACH OF CHILDREN

Keep out reach of children.If swallowed get medical help or contact a Poison Control Center right away

INDICATIONS AND USAGE

Stop useif rash or irritation occurs

Warnings

For external use only. Do not useon broken skin

DIrections

apply before bed and again in morning

apply to underarm only

Inactive ingredients

Cyclopentasiloxane, Stearyl Alcohol, PPG-14 Butyl Ether, Dicaprylyl Carbonate, Fragrance, Hydrogenated Castor Oil, Isopropyl Myristate, Lauryl Methacrylate/Glycol Dimethacrylate Crosspolymer, PEG-8 Distearate, Silica, Propylene Glycol, Ethylhexylglycerin, Maranta Arundinacea Root Extract, Coconut Alkanes, Charcoal Powder, Octenidine Hydrochloride, Coco-Caprylate/Caprate.

PACKAGE LABEL

Carpe

Clinical Grade

Underarm

Antiperspirant

Daily Use Fresh Linen Scent

Net Wt 2 OZ (58 G)